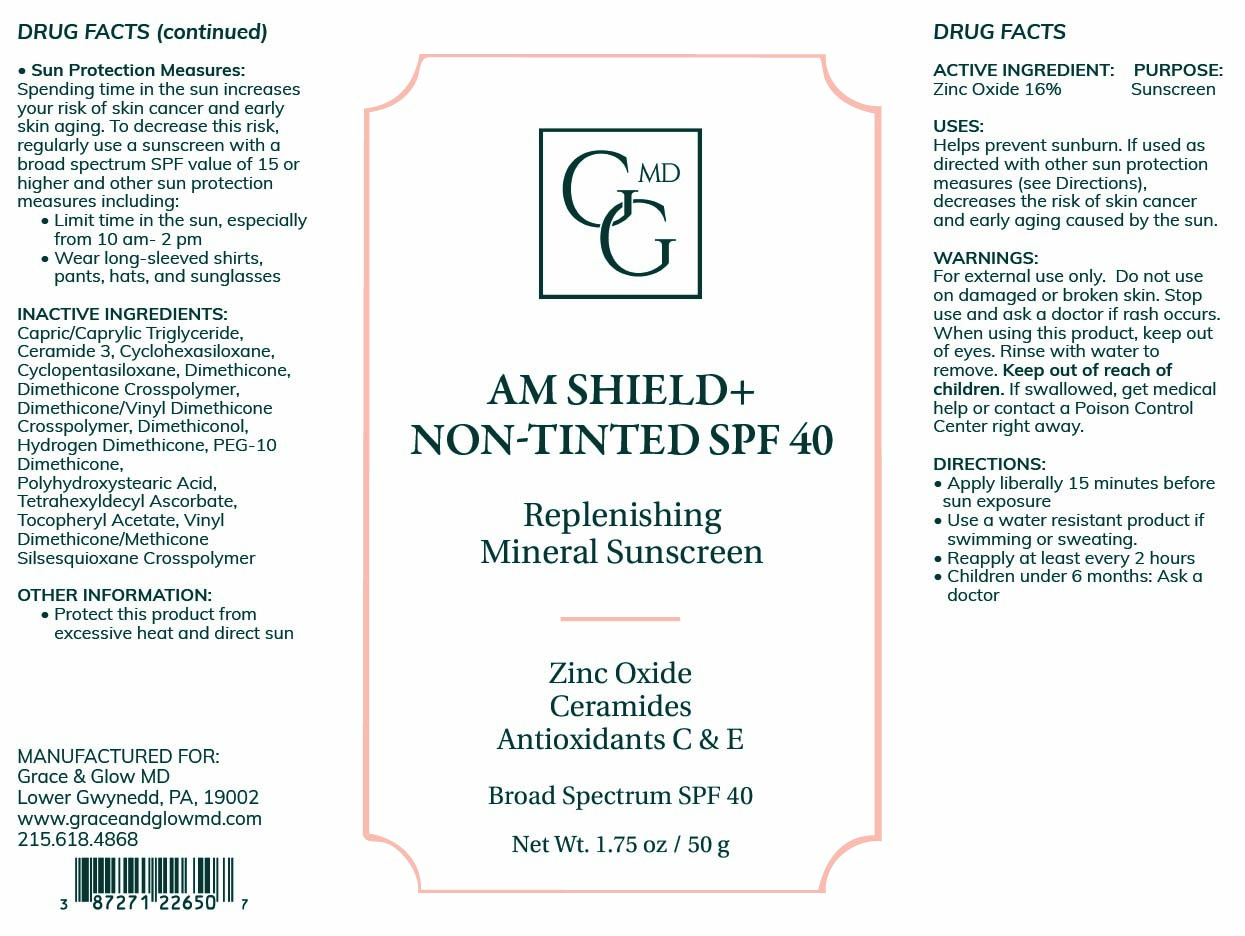 DRUG LABEL: AM Shield plus
NDC: 87271-226 | Form: CREAM
Manufacturer: Grace and Glow MD LLC
Category: otc | Type: HUMAN OTC DRUG LABEL
Date: 20260225

ACTIVE INGREDIENTS: ZINC OXIDE 160 mg/1 g
INACTIVE INGREDIENTS: CYCLOPENTASILOXANE; CERAMIDE 3; DIMETHICONOL (2000 CST); DIMETHICONE/VINYL DIMETHICONE CROSSPOLYMER (SOFT PARTICLE); VINYL DIMETHICONE/METHICONE SILSESQUIOXANE CROSSPOLYMER; PEG-10 DIMETHICONE (600 CST); HYDROGEN DIMETHICONE (20 CST); ALPHA-TOCOPHEROL ACETATE; DIMETHICONE; CAPRYLIC/CAPRIC TRIGLYCERIDE; DIMETHICONE CROSSPOLYMER; CYCLOHEXASILOXANE; POLYHYDROXYSTEARIC ACID (2300 MW); TETRAHEXYLDECYL ASCORBATE

ACTIVE INGREDIENT

Zinc Oxide 16%

PURPOSE

Sunscreen

INDICATIONS AND USAGE

Helps Prevent Sunburn. If used as directed with other sun protection measures (see “Directions”), decreases the risk of skin cancer and early skin aging caused by the sun.

WARNINGS

For external use only. Do not use on broken or damaged skin. Stop use and ask a doctor if rash occurs. When using this product, keep out of eyes. Rinse with water to remove. Keep out of reach of children. If swallowed, get medical help or contact a poison control center right away.

Keep out of reach of children

DOSAGE AND ADMINISTRATION

Apply liberally 15 minutes before sun exposure. Use a water-resistant product if swimming or sweating. Reapply at least every 2 hours. Children under 6 months: Ask a doctor. Sun Protection Measures: Spending time in the sun increases your risk of skin cancer and early skin aging. To decrease this risk, regularly use a sunscreen with a Broad-Spectrum SPF value of 15 or higher and other sun protection measures including: Limit time in the sun, especially from 10 a.m. - 2 p.m. Wear long-sleeved shirts, pants, hats and sunglasses.

INACTIVE INGREDIENT

Caprylic/Capric Triglyceride, Ceramide 3, Cyclohexasiloxane, Cyclopentasiloxane, Dimethicone, Dimethicone Crosspolymer, Dimethicone/Vinyl Dimethicone Crosspolymer, Dimethiconol, Hydrogen Dimethicone, PEG-10 Dimethicone, Polyhydroxystearic Acid, Tetrahexyldecyl Ascorbate, Tocopheryl Acetate, Vinyl Dimethicone/Methicone Silsesquioxane Crosspolymer

OTHER SAFETY INFORMATION

Protect this product from excessive heat and direct sun